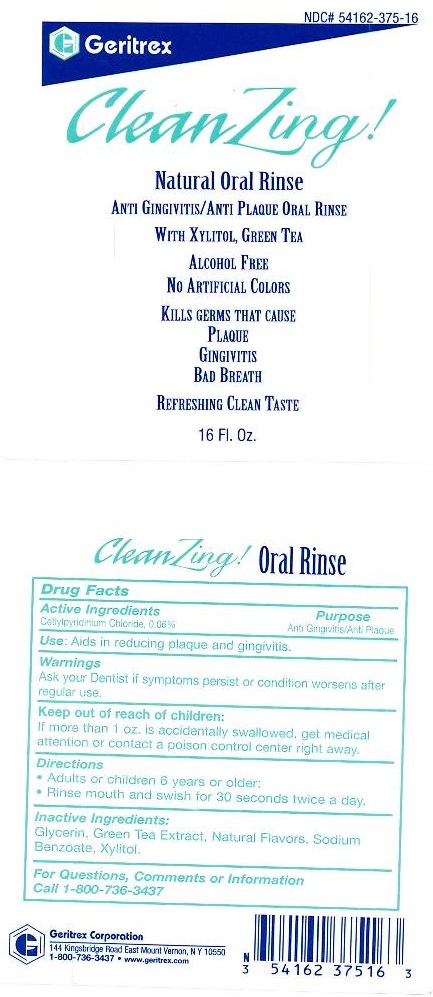 DRUG LABEL: CleanZing
NDC: 54162-375 | Form: SOLUTION
Manufacturer: Geritrex LLC
Category: otc | Type: HUMAN OTC DRUG LABEL
Date: 20151229

ACTIVE INGREDIENTS: CETYLPYRIDINIUM CHLORIDE 0.283 g/473 mL
INACTIVE INGREDIENTS: GLYCERIN; GREEN TEA LEAF; SODIUM BENZOATE; XYLITOL

CleanZing

Active Ingredient:

Cetylpyridium Chloride 0.06%

Purpose:

Anti gingivitis/Anti plaque

Use:

Aids in reducing plaque and gingivitis

Warnings:

Ask your dentist if symptoms persist or condition worsens after regular use.

Keep out of reach of children:

If more than 1 oz. is accidentally swallowed, get medical attention or contact a poison control center right away.

Directions:

- Adults or children 6 years or older:
- Rinse mouth and swish for 30 seconds twice a day

Inactive Ingredients:

Glycerin, Green Tea Extract, Natural Flavors, Sodium Benzoate, Xylitol